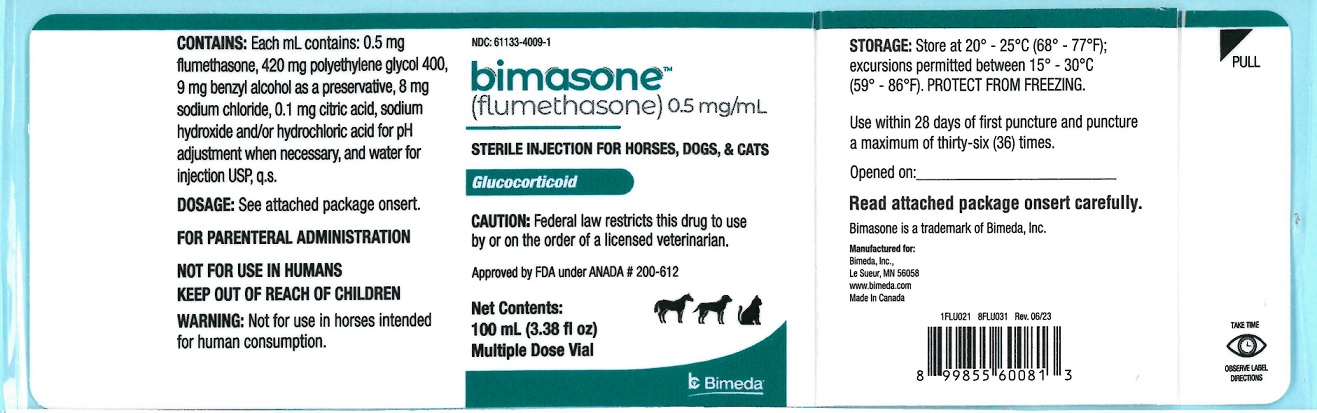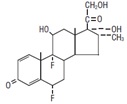 DRUG LABEL: Bimasone
NDC: 61133-4009 | Form: INJECTION, SOLUTION
Manufacturer: Bimeda, Inc.
Category: animal | Type: PRESCRIPTION ANIMAL DRUG LABEL
Date: 20240423

ACTIVE INGREDIENTS: FLUMETHASONE .5 mg/1 mL
INACTIVE INGREDIENTS: POLYETHYLENE GLYCOL 400 420 mg/1 mL; benzyl alcohol 9 mg/1 mL; SODIUM CHLORIDE 8 mg/1 mL

DESCRIPTION

BimasoneTM
(flumethasone) 0.5 mg/mL
STERILE INJECTION FOR HORSES, DOGS, & CATS
Glucocorticoid

CAUTION
Federal law restricts this drug to use by or on the order of a licensed veterinarian.

GENERAL
Flumethasone is a chemical modification of prednisolone which possesses greater anti-inflammatory and gluconeogenic properties than the parent compound when compared on an equivalent basis. Due to the potency of Bimasone, dosage recommendations should be consulted prior to drug administration. Chemically, it is 6α, 9α-difluoro-16α methylprednisolone.
The structural formula is as follows:

DESCRIPTION

The active ingredient of Bimasone is flumethasone which occurs as a white to creamy white, odorless,
crystalline powder. The appearance of Bimasone is a clear colorless to slightly yellowish mobile liquid.
Each mL of the injectable preparation contains 0.5 mg flumethasone, 420 mg polyethylene glycol 400, 9 mg benzyl alcohol as a preservative, 8 mg sodium chloride, 0.1 mg citric acid, sodium hydroxide and/or hydrochloric acid for pH adjustment when necessary, and water for injection USP, q.s.

CLINICAL PHARMACOLOGY
Flumethasone has been reported (1) to possess 700 times the glucocorticoid activity of cortisol (hydrocortisone) as measured in the liver glycogen deposition assay in the rat; 120 times that of cortisol in the cotton pellet assay in the rat; and also in the same animal, shows a net excretion of sodium.
In similar tests in rats, another report (2) showed flumethasone 730 times more potent than cortisol in the granuloma inhibition assay and 165 times the activity of cortisol in the glycogen deposition assay. The same report showed that in man, the compound possessed 7.8 times the potency of prednisolone.
An additional report (3) indicated that flumethasone possessed 677 times the potency of cortisol in the liver glycogen deposition test in the rat, and 30, 25, and 31 times respectively, the eosinopenic, hyperglycemic and antirheumatic potency of cortisol, as measured in man.
Veterinary experimental studies utilizing the eosinophil depression test in normal dogs and blood glucose elevation and eosinophil depression in normal cattle as parameters of drug activity, in comparison tests involving prednisone and dexamethasone, indicate that flumethasone possesses greater anti-inflammatory and gluconeogenic activity than these compounds, on an equivalent basis.
Clinical evidence of drug potency obtained during evaluation of the compound and based upon effective
drug dosage levels further substantiates the above experimental findings.

General Effects of Adrenocorticoids
The adrenocorticoids are divided into two main classes: mineralocorticoids and glucocorticoids, based on their major physiologic and pharmacologic actions.
Mineralocorticoids such as the naturally occurring desoxycorticosterone and aldosterone are mainly
concerned with hydration, sodium and potassium regulation and the normal renal glomerular filtration of these two electrolytes. The mineralocorticoids have little if any effect as anti-inflammatory agents, and are not widely used in medicine.
Glucocorticoids include the naturally occurring compounds, cortisone and hydrocortisone.
Their major effects are as follows:

1. Increase protein catabolism and gluconeogenesis.
2. Depressionof lymphoid tissues, fibroblasts and eosinophils.
3. Increase the sense of well being and tolerance to pain.
4. Depress thyroid function and anterior pitutiary function through reciprocal influences.
5. Influence vasoconstrictive response of the circulatory system to norepinephrine, helping to maintain blood pressure.
6. Increase renal flow.
7. Influence gastric HCl and pepsin production.
8. Reduces the secretion of mucus from respiratory and enteric mucosa.
9. Affect to some degree sodium retention and potassium excretion.
10. Stimulate erythropoiesis and myelopoiesis.

Synthetic analogues of cortisone and hydrocortisone containing a double bond between carbon 1 and 2 of the corticosteroid nucleus, resulted in compounds with a greatly decreased effect on electrolyte metabolism.
Additional molecular changes present in other synthetic corticoids presently used in medicine such as
methylation at carbons 6 or 16 and hydroxylation at carbon 16, have led to a further decrease in electrolyte imbalance noted with the naturally occurring glucocorticoids. Fluorination at carbon 6 and/or 9 have led to a marked increase in anti-inflammatory activity.
The synthetic glucocorticoids exhibit a marked increase in potency in that a smaller amount of drug is required to elicit the same effects seen only with large amounts of the natural glucocorticoids. It is also noted that the synthetic analogues persist for a longer period of time in the body which is believed due to their slower metabolism and excretion.

INDICATIONS
Bimasone is recommended for the various rheumatic, allergic, dermatologic and other disease states which are known to be responsive to the anti-inflammatory corticoids.

Equine Indications

1. Musculoskeletal conditions due to inflammation, where permanent structural changes do not exist,
such as bursitis, carpitis, osselets and myositis. Following therapy an appropriate period of rest should be instituted to allow a more normal return to function of the affected part.

2. In allergic states such as hives, urticaria and insect bites.

Canine Indications

1. Musculoskeletal conditions due to inflammation of muscles or joints and accessory structures, where
permanent structural changes do not exist, such as arthritis, osteoarthritis, the disc syndrome and
myositis. In septic arthritis appropriate antibacterial therapy should be concurrently administered.

2. In certain acute and chronic dermatoses of varying etiology to help control the pruritus, irritation and
inflammation associated with these conditions. The drug has proven useful in otitis externa in conjunction with topical medication for similar reasons.

3. In allergic states such as hives, urticaria and insect bites.

4. Shock and shock-like states, (4) by intravenous administration.

Feline Indications

1. In certain acute and chronic dermatoses of varying etiology to help control the pruritus,
irritation and inflammation associated with these conditions.

ADMINISTRATION AND DOSAGE
Bimasone is recommended for administration by injection using various routes depending on the
animal species and conditions under treatment. Injection should be accomplished slowly, with the
drug at or near body temperature.

The following recommended dosages should be used as therapeutic guides. Each animal should be treated on an individual basis and dosage adjusted according to the response noted.

Dosage of Bimasone:

Equine: 1.25 to 2.5 mg daily by intravenous, intramuscular or intra-articular injection. If
necessary, the dose may be repeated.

Canine: 0.0625 to 0.25 mg daily by intravenous, intramuscular or subcutaneous injection. If
necessary, the dose may be repeated. With chronic conditions, the preceding doses may
be used and oral maintenance therapy with flumethasone tablets instituted at a daily
dose of 0.0625 to 0.25 mg.
lntralesional dosages in the dog have ranged from 0.125 to 1 mg depending on the size and
location of the lesion under treatment.
Intra-articular dosages in the dog have ranged from 0.166 to 1 mg depending on the severity of the condition under treatment and the size of the involved joint.
Feline: 0.03125 to 0.125 mg by intravenous, intramuscular or subcutaneous injection. If necessary, the dose may be repeated. With chronic conditions, the preceding injectable doses may be used and oral maintenance therapy with flumethasone tablets instituted at a daily dosage of 0.03125 to 0.125 mg.
NOTE: The use of a microsyringe or standard tuberculin syringe may facilitate the accurate
administration of small amounts of the drug.

If desired, therapy with Bimasone may be substituted for other corticoids by the appropriate adjustment of dose levels.

PRECAUTIONS
The usual precautions and contraindications for adrenocorticoid hormones are applicable with this compound. The close observation of animals under treatment with this drug is necessary, since the usual signs of adrenocorticoid overdosage which include sodium retention, potassium loss, fluid retention, weight gain, etc., may not be readily observed.
Use of corticosteroids depending on dose duration and specific steroid may result in inhibition of endogenous steroid production following drug withdrawal. In patients presently receiving or recently withdrawn from systemic steroid treatments, therapy with a rapidly acting corticosteroid should be considered in unusually stressful situations.
Experimentally, it has been demonstrated that corticosteroids especially at high dose levels may result in delayed wound healing. An increase in the incidence of osteoporosis may be noted, mainly in the elderly, with the prolonged use of these compounds. Their use in older dogs and cats, during the healing stages of a bone fracture is not indicated for this reason. The intra-articular injection in leg injuries of the horse may produce osseous metaplasia.
If side effects occur, the veterinarian should be prepared to take the necessary steps to correct them, which consist of temporarily discontinuing therapy with the drug until the side effects disappear, when therapy may be resumed at a lower dose level.
When long-term therapy with corticosteroids is used, as is necessary on occasion in the dog and cat, the dose should be individually adjusted so that the minimum maintenance dose (which will keep the condition being treated under control) is desirable. In dogs and cats on long-term therapy with these drugs, a protein-rich diet is useful to counteract nitrogen loss if it should occur.
Similarly, a small amount of potassium chloride daily in the diet will counteract excessive potassium loss if this is present. Some natural dietary sources of potassium include dry nonfat milk solids, citrus juice, bran flakes, meat, fish and light cane molasses.
Bimasone may be administered to animals with bacterial diseases provided that specific and appropriate antibacterial therapy with antibiotic is administered simultaneously. In the absence of specific concomitant antimicrobial therapy, the prolonged use of corticosteroids is likely to lead to the spread of pathogenic microorganisms. The use of corticosteroids in such situations is not indicated. It should be borne in mind that flumethasone, like cortisone, through its anti-inflammatory action, may mask the usual signs of an infection such as pyrexia, inappetence, lassitude, etc. In the course of therapy with Bimasone, should the question of determining the presence of an infectious disease arise, the drug should be withheld temporarily until a diagnosis or rediagnosis establishes the facts.
SIDE EFFECTS
Side effects such as SAP and SGPT(ALT) enzyme elevations, weight loss, anorexia, polydipsia and polyuria
have occurred following parenteral or systemic use of synthetic corticosteroids. In dogs, vomiting and diarrhea, and Cushing's syndrome have been reported in association with prolonged or repeated steroid therapy.
Corticosteroids reportedly cause laminitis in horses.

WARNINGS
Clinical and experimental data have demonstrated that corticosteroids administered orally or by injection to animals may induce the first stage of parturition when administered during the last trimester of pregnancy and may precipitate premature parturition followed by dystocia, fetal death, retained placenta and metritis.
Additionally, corticosteroids administered to dogs, rabbits and rodents during pregnancy have resulted in cleft palate in offspring. Corticosteroids administered to dogs during pregnancy have also resulted in other congenital anomalies, including deformed forelegs, phocomelia and anasarca.

CONTRAINDICATIONS
Do not use in viral infections. Except for emergency therapy, do not use in animals with tuberculosis, chronic nephritis, cushingoid syndrome and peptic ulcers. Existence of congestive heart failure, diabetes and osteoporosis are relative contraindications.

CONTACT INFORMATION
To report suspected adverse drug events, for technical assistance or to obtain a copy of the Safety Data Sheet (SDS), contact Bimeda, Inc. at 1-888-524-6332. For additional information about adverse drug experience reporting for animal drugs, contact FDA at 1-888-FDA-VETS or http://www.fda.gov/reportanimalae

HOW SUPPLIED

Bimasone is supplied in 100 mL vials.

STORAGE
Store at 20° - 25°C (68° - 77°F); excursions permitted between 15° - 30°C (59° - 86°F). PROTECT FROM
FREEZING. Use within 28 days of first puncture and puncture a maximum of thirty-six (36) times.

REFERENCES
1. Fried, J.: “Biological Activities of Steroids in Relation to Cancer." Edited by G. Pincus and E. Volmer, Academic Press, New York and London, (1960), 9-24.
2. Boland, E.W.: Am. J. Med. 31, (Oct. 1961), 581-590.
3. Ringler, I., West, D., Dulin, W.E. and Boland, E.W.: Metabolism, Vol. 13, No. 1; (Jan. 1964), 37-44.
4. Lillehei, R.C., Longerbeam, J.K., Block, J.H. and Mannox, W.G.: Clin. Pharmacol. Ther. 5, (Jan.-Feb. 1964).

Approved by FDA under ANADA # 200-612